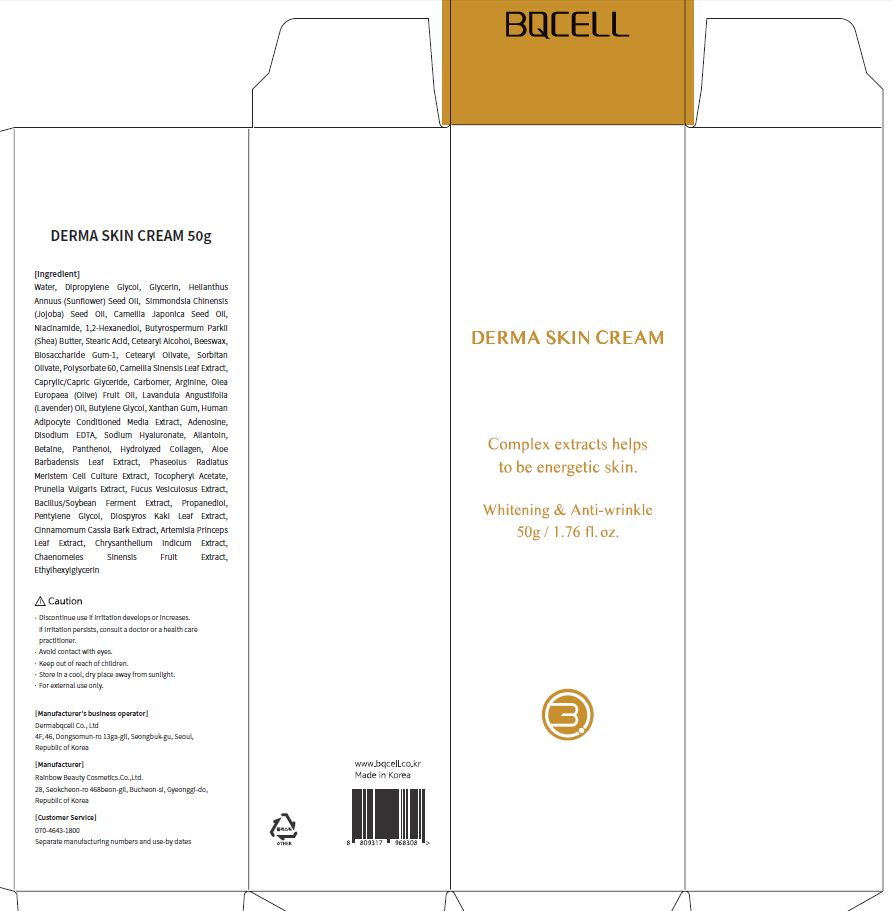 DRUG LABEL: DERMA SKINCREAM
NDC: 82665-0003 | Form: CREAM
Manufacturer: Dermabqcell Co., Ltd.
Category: otc | Type: HUMAN OTC DRUG LABEL
Date: 20221011

ACTIVE INGREDIENTS: ADENOSINE 2 g/100 g; NIACINAMIDE 0.04 g/100 g
INACTIVE INGREDIENTS: WATER

ACTIVE INGREDIENT

adenosine, niacinamide

INACTIVE INGREDIENT

Water, Dipropylene Glycol, Glycerin, Helianthus Annuus (Sunflower) Seed Oil,
Simmondsia Chinensis (Jojoba) Seed Oil, Camellia Japonica Seed Oil, Niacinamide,
1,2-Hexanediol, Butyrospermum Parkii (Shea) Butter, Stearic Acid, Cetearyl Alcohol,
Beeswax, Biosaccharide Gum-1, Cetearyl Olivate, Sorbitan Olivate, Polysorbate 60,
Camellia Sinensis Leaf Extract, Caprylic/Capric Glyceride, Carbomer, Arginine, Olea
Europaea (Olive) Fruit Oil, Lavandula Angustifolia (Lavender) Oil, Butylene Glycol,
Xanthan Gum, Human Adipocyte Conditioned Media Extract, Adenosine, Disodium
EDTA, Sodium Hyaluronate, Allantoin, Betaine, Panthenol, Hydrolyzed Collagen,
Aloe Barbadensis Leaf Extract, Phaseolus Radiatus Meristem Cell Culture Extract,
Tocopheryl Acetate, Prunella Vulgaris Extract, Fucus Vesiculosus Extract,
Bacillus/Soybean Ferment Extract, Propanediol, Pentylene Glycol, Diospyros Kaki
Leaf Extract, Cinnamomum Cassia Bark Extract, Artemisia Princeps Leaf Extract,
Chrysanthellum Indicum Extract, Chaenomeles Sinensis Fruit Extract,
Ethylhexylglycerin

PURPOSE

wrinkle care, whitening

Keep out of reach of children

INDICATIONS AND USAGE

apply proper amount to the skin

WARNINGS

discontinue use if irritation develops or increases

if irritation persists, consult a doctor or a health care practitioner

avoid contact with eyes

keep out of reach of children

DOSAGE AND ADMINISTRATION

For external use only